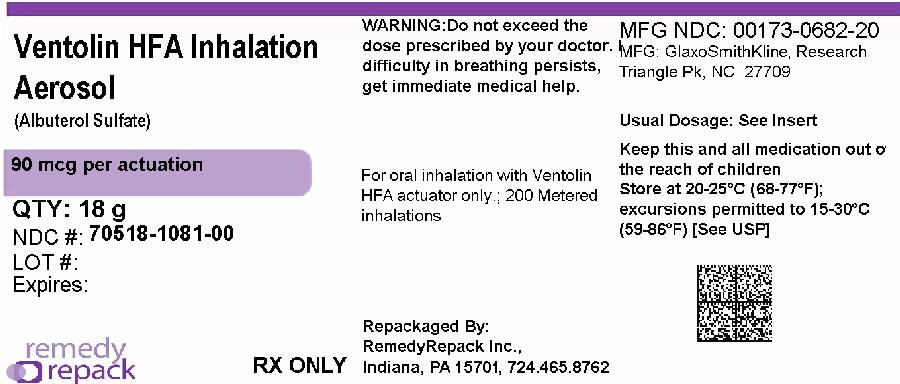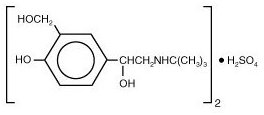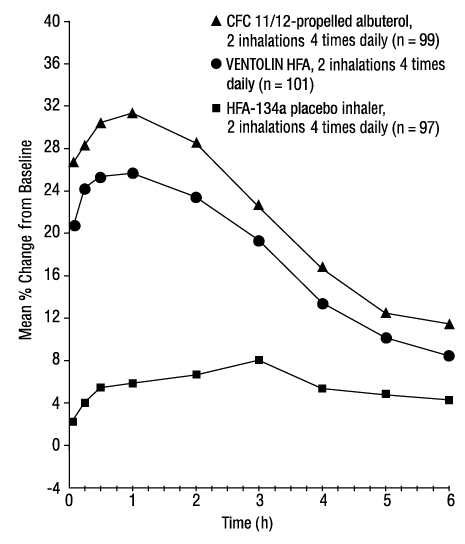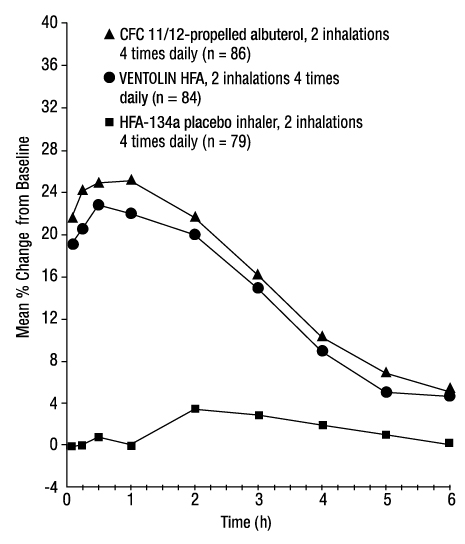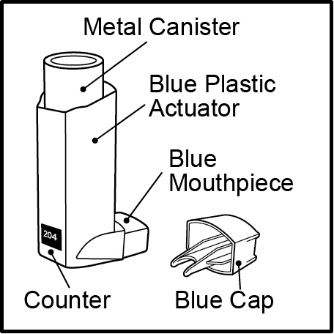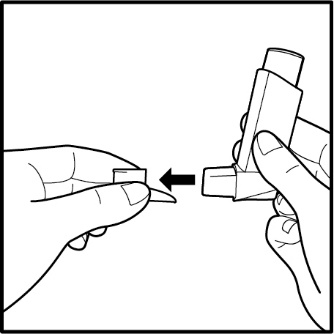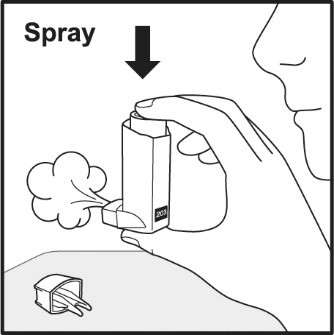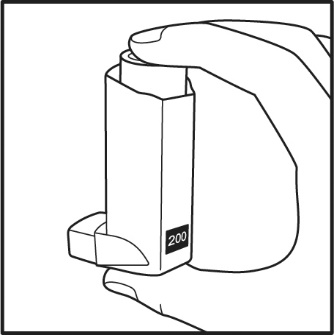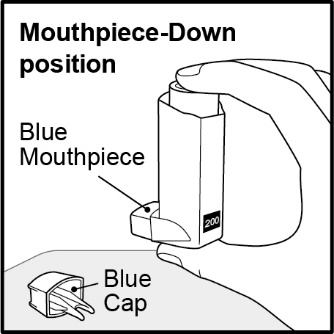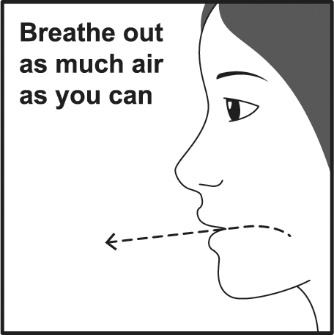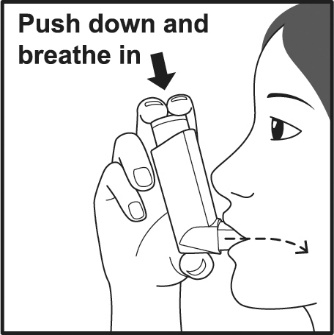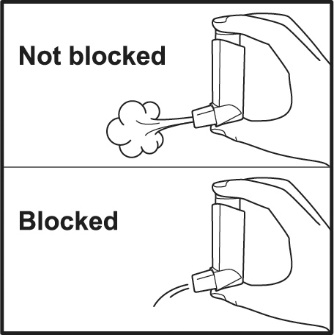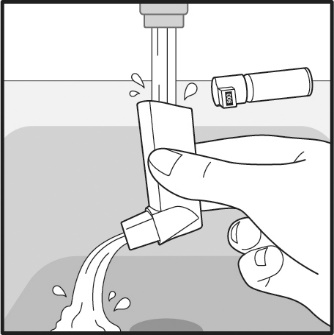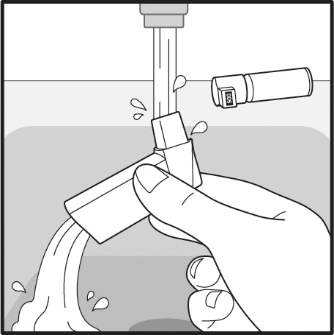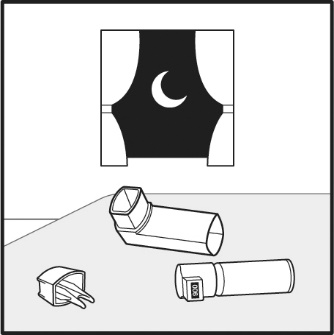 DRUG LABEL: VENTOLIN
NDC: 70518-1081 | Form: AEROSOL, METERED
Manufacturer: REMEDYREPACK INC.
Category: prescription | Type: HUMAN PRESCRIPTION DRUG LABEL
Date: 20260114

ACTIVE INGREDIENTS: ALBUTEROL SULFATE 90 ug/1 1
INACTIVE INGREDIENTS: NORFLURANE

HIGHLIGHTS OF PRESCRIBING INFORMATION

These highlights do not include all the information needed to use VENTOLIN HFA safely and effectively. See full prescribing information for VENTOLIN HFA.
VENTOLIN HFA (albuterol sulfate inhalation aerosol), for oral inhalation use
Initial U.S. Approval: 1981

1 INDICATIONS AND USAGE

VENTOLIN HFA is a beta2-adrenergic agonist indicated for:

- Treatment or prevention of bronchospasm in adult and pediatric patients aged 4 years and older with reversible obstructive airway disease. (1.1)
- Prevention of exercise-induced bronchospasm in adult and pediatric patients aged 4 years and older. (1.2)

2 DOSAGE AND ADMINISTRATION

- For oral inhalation only. (2)
- Treatment or prevention of bronchospasm in adult and pediatric patients aged 4 years and older: 2 inhalations by oral inhalation every 4 to 6 hours. For some patients, 1 inhalation every 4 hours may be sufficient. (2.1)
- Prevention of exercise-induced bronchospasm in adult and pediatric patients aged 4 years and older: 2 inhalations by oral inhalation 15 to 30 minutes before exercise. (2.2)
- Priming information: Prime VENTOLIN HFA before using for the first time, when the inhaler has not been used for more than 2 weeks, or when the inhaler has been dropped. To prime VENTOLIN HFA, release 4 sprays into the air away from the face, shaking well before each spray. (2.3)
- Cleaning information: At least once a week, wash the actuator with warm water and let it air-dry completely. (2.3)

3 DOSAGE FORMS AND STRENGTHS

Inhalation aerosol: 108 mcg albuterol sulfate (90 mcg albuterol base) per actuation. (3)

4 CONTRAINDICATIONS

Hypersensitivity to any ingredient. (4)

5 WARNINGS AND PRECAUTIONS

- Life-threatening paradoxical bronchospasm may occur. Discontinue VENTOLIN HFA immediately and institute alternative therapy. (5.1)
- Need for more doses of VENTOLIN HFA than usual may be a sign of deterioration of asthma and requires reevaluation of treatment. (5.2)
- VENTOLIN HFA is not a substitute for corticosteroids. (5.3)
- Cardiovascular effects may occur. Use with caution in patients sensitive to sympathomimetic drugs and patients with cardiovascular or convulsive disorders. (5.4, 5.7)
- Excessive use may be fatal. Do not exceed recommended dose. (5.5)
- Immediate hypersensitivity reactions may occur. Discontinue VENTOLIN HFA immediately. (5.6)
- Hypokalemia and changes in blood glucose may occur. (5.7, 5.8)

6 ADVERSE REACTIONS

Most common adverse reactions (incidence ≥3%) are throat irritation, viral respiratory infections, upper respiratory inflammation, cough, and musculoskeletal pain. (6.1)

To report SUSPECTED ADVERSE REACTIONS, contact GlaxoSmithKline at 1-888-825-5249 or FDA at 1-800-FDA-1088 or www.fda.gov/medwatch.

7 DRUG INTERACTIONS

- Beta-blockers: Use with caution. May block bronchodilatory effects of beta-agonists and produce severe bronchospasm. (7.1)
- Diuretics: Use with caution. Electrocardiographic changes and/or hypokalemia associated with non–potassium-sparing diuretics may worsen with concomitant beta-agonists. (7.2)
- Digoxin: May decrease serum digoxin levels. Consider monitoring digoxin levels. (7.3)
- Monoamine oxidase inhibitors and tricyclic antidepressants: Use with extreme caution. May potentiate effect of albuterol on vascular system. (7.4)

FULL PRESCRIBING INFORMATION

1 INDICATIONS AND USAGE

1.1 Bronchospasm

VENTOLIN HFA is indicated for the treatment or prevention of bronchospasm in adult and pediatric patients aged 4 years and older with reversible obstructive airway disease.

1.2 Exercise-Induced Bronchospasm

VENTOLIN HFA is indicated for the prevention of exercise-induced bronchospasm in adult and pediatric patients aged 4 years and older.

2 DOSAGE AND ADMINISTRATION

2.1 Recommended Dosage for Bronchospasm (Acute Episodes or Symptoms Associated with Bronchospasm)

Adult and pediatric patients aged 4 years and older: 2 inhalations by oral inhalation repeated every 4 to 6 hours; in some patients, 1 inhalation every 4 hours may be sufficient. More frequent administration or a greater number of inhalations is not recommended.

2.2 Recommended Dosage for Prevention of Exercise-Induced Bronchospasm

Adult and pediatric patients aged 4 years and older: 2 inhalations by oral inhalation 15 to 30 minutes before exercise.

2.3 Administration Information

VENTOLIN HFA should be administered by the orally inhaled route only.

Priming

Priming VENTOLIN HFA is essential to ensure appropriate albuterol content in each actuation. Prime VENTOLIN HFA before using for the first time, when the inhaler has not been used for more than 2 weeks, or when the inhaler has been dropped. To prime VENTOLIN HFA, release 4 sprays into the air away from the face, shaking well before each spray. Avoid spraying in eyes.

Cleaning

To ensure proper dosing and to prevent actuator orifice blockage, wash the actuator with warm water and let it air-dry completely at least once a week.

3 DOSAGE FORMS AND STRENGTHS

Inhalation aerosol: 108 mcg of albuterol sulfate (90 mcg of albuterol base) from the mouthpiece per actuation. Blue plastic inhaler with a blue cap containing a pressurized metered-dose aerosol canister containing 60 or 200 metered inhalations and fitted with a counter.

4 CONTRAINDICATIONS

VENTOLIN HFA is contraindicated in patients with a history of hypersensitivity to any of the ingredients [see Warnings and Precautions (5.6), Description (11)] .

5 WARNINGS AND PRECAUTIONS

5.1 Paradoxical Bronchospasm

VENTOLIN HFA can produce paradoxical bronchospasm, which may be life threatening. If paradoxical bronchospasm occurs following dosing with VENTOLIN HFA, it should be discontinued immediately and alternative therapy should be instituted. It should be recognized that paradoxical bronchospasm, when associated with inhaled formulations, frequently occurs with the first use of a new canister.

5.2 Deterioration of Asthma

Asthma may deteriorate acutely over a period of hours or chronically over several days or longer. If the patient needs more doses of VENTOLIN HFA than usual, this may be a marker of destabilization of asthma and requires reevaluation of the patient and treatment regimen, giving special consideration to the possible need for anti-inflammatory treatment, e.g., corticosteroids.

5.3 Use of Anti-inflammatory Agents

The use of beta-adrenergic agonist bronchodilators alone may not be adequate to control asthma in many patients. Early consideration should be given to adding anti-inflammatory agents, e.g., corticosteroids, to the therapeutic regimen.

5.4 Cardiovascular Effects

VENTOLIN HFA, like all other beta2-adrenergic agonists, can produce clinically significant cardiovascular effects in some patients such as changes in pulse rate or blood pressure. If such effects occur, VENTOLIN HFA may need to be discontinued. In addition, beta-agonists have been reported to produce electrocardiogram (ECG) changes, such as flattening of the T wave, prolongation of the QTc interval, and ST segment depression. The clinical relevance of these findings is unknown. Therefore, VENTOLIN HFA, like all other sympathomimetic amines, should be used with caution in patients with underlying cardiovascular disorders, especially coronary insufficiency, cardiac arrhythmias, and hypertension.

5.5 Do Not Exceed Recommended Dose

Fatalities have been reported in association with excessive use of inhaled sympathomimetic drugs in patients with asthma. The exact cause of death is unknown, but cardiac arrest following an unexpected development of a severe acute asthmatic crisis and subsequent hypoxia is suspected.

5.6 Hypersensitivity Reactions, including Anaphylaxis

Immediate hypersensitivity reactions (e.g., urticaria, angioedema, rash, bronchospasm, hypotension), including anaphylaxis, may occur after administration of VENTOLIN HFA [see Contraindications (4)] .

5.7 Coexisting Conditions

VENTOLIN HFA, like other sympathomimetic amines, should be used with caution in patients with convulsive disorders, hyperthyroidism, or diabetes mellitus and in patients who are unusually responsive to sympathomimetic amines. Large doses of intravenous albuterol have been reported to aggravate preexisting diabetes mellitus and ketoacidosis.

5.8 Hypokalemia

Beta-adrenergic agonist medicines may produce significant hypokalemia in some patients, possibly through intracellular shunting, which has the potential to produce adverse cardiovascular effects [see Clinical Pharmacology (12.1)] . The decrease in serum potassium is usually transient, not requiring supplementation.

6 ADVERSE REACTIONS

The following clinically significant adverse reactions are described elsewhere in the labeling:

- Paradoxical bronchospasm [see Warnings and Precautions (5.1)]
- Cardiovascular effects [see Warnings and Precautions (5.4)]
- Hypersensitivity reactions, including anaphylaxis [see Warnings and Precautions (5.6)]
- Hypokalemia [see Warnings and Precautions (5.8)]

6.1 Clinical Trials Experience

Because clinical trials are conducted under widely varying conditions, adverse reaction rates observed in the clinical trials of a drug cannot be directly compared with rates in the clinical trials of another drug and may not reflect the rates observed in practice.

The safety data described below reflects exposure to VENTOLIN HFA in 248 subjects treated with VENTOLIN HFA in 3 placebo-controlled clinical trials of 2 to 12 weeks’ duration. The data from adults and adolescents is based upon 2 clinical trials in which 202 subjects with asthma aged 12 years and older were treated with VENTOLIN HFA 2 inhalations 4 times daily for 12 weeks’ duration. The adult/adolescent population was 92 female, 110 male and 163 white, 19 black, 18 Hispanic, 2 other. The data from pediatric subjects are based upon 1 clinical trial in which 46 subjects with asthma aged 4 to 11 years were treated with VENTOLIN HFA 2 inhalations 4 times daily for 2 weeks’ duration. The population was 21 female, 25 male and 25 white, 17 black, 3 Hispanic, 1 other.

Adult and Adolescent Subjects Aged 12 Years and Older

The two 12-week, randomized, double-blind trials in 610 adult and adolescent subjects with asthma that compared VENTOLIN HFA, a CFC 11/12-propelled albuterol inhaler, and an HFA-134a placebo inhaler. Overall, the incidence and nature of the adverse reactions reported for VENTOLIN HFA and a CFC 11/12-propelled albuterol inhaler were comparable. Table 1 lists the incidence of all adverse reactions (whether considered by the investigator to be related or unrelated to drug) from these trials that occurred at a rate of ≥3% in the group treated with VENTOLIN HFA and more frequently in the group treated with VENTOLIN HFA than in the HFA-134a placebo inhaler group.

Table 1. Adverse Reactions with VENTOLIN HFA with ≥3% Incidence and More Common than Placebo in Adult and Adolescent Subjects
Adverse Reaction | Percent of Subjects
Adverse Reaction | VENTOLIN HFA; (n = 202); % | CFC 11/12-Propelled; Albuterol Inhaler; (n = 207); % | Placebo HFA-134a; (n = 201); %
Ear, nose, and throat
- Throat irritation | 10 | 6 | 7
- Upper respiratory inflammation | 5 | 5 | 2
Lower respiratory
- Viral respiratory infections | 7 | 4 | 4
- Cough | 5 | 2 | 2
Musculoskeletal
- Musculoskeletal pain | 5 | 5 | 4

Adverse reactions reported by <3% of the adult and adolescent subjects receiving VENTOLIN HFA and by a greater proportion of subjects receiving VENTOLIN HFA than receiving HFA-134a placebo inhaler and that have the potential to be related to VENTOLIN HFA include diarrhea, laryngitis, oropharyngeal edema, cough, lung disorders, tachycardia, and extrasystoles. Palpitations and dizziness have also been observed with VENTOLIN HFA.

Pediatric Subjects Aged 4 to 11 Years

Results from the 2-week clinical trial in pediatric subjects with asthma aged 4 to 11 years showed that this pediatric population had an adverse reaction profile similar to that of the adult and adolescent populations.

Three trials have been conducted to evaluate the safety and efficacy of VENTOLIN HFA in subjects between birth and 4 years of age. The results of these trials did not establish the efficacy of VENTOLIN HFA in this age group [see Use in Specific Populations (8.4)]. Since the efficacy of VENTOLIN HFA has not been demonstrated in children between birth and 48 months of age, the safety of VENTOLIN HFA in this age group cannot be established. However, the safety profile observed in the pediatric population younger than 4 years was comparable to that observed in the older pediatric subjects and in adults and adolescents. Where adverse reaction incidence rates were greater in subjects younger than 4 years compared with older subjects, the higher incidence rates were noted in all treatment arms, including placebo. These adverse reactions included upper respiratory tract infection, nasopharyngitis, pyrexia, and tachycardia.

6.2 Postmarketing Experience

In addition to adverse reactions reported from clinical trials, the following adverse reactions have been identified during postapproval use of albuterol sulfate. Because these reactions are reported voluntarily from a population of uncertain size, it is not always possible to reliably estimate their frequency or establish a causal relationship to drug exposure. These events have been chosen for inclusion due to either their seriousness, frequency of reporting, or causal connection to albuterol or a combination of these factors.

Cases of paradoxical bronchospasm, hoarseness, arrhythmias (including atrial fibrillation, supraventricular tachycardia), and hypersensitivity reactions (including urticaria, angioedema, rash) have been reported after the use of VENTOLIN HFA.

In addition, albuterol, like other sympathomimetic agents, can cause adverse reactions such as hypokalemia, hypertension, peripheral vasodilatation, angina, tremor, central nervous system stimulation, hyperactivity, sleeplessness, headache, muscle cramps, drying or irritation of the oropharynx, and metabolic acidosis.

7 DRUG INTERACTIONS

Other short-acting sympathomimetic aerosol bronchodilators should not be used concomitantly with albuterol. If additional adrenergic drugs are to be administered by any route, they should be used with caution to avoid deleterious cardiovascular effects.

7.1 Beta-Adrenergic Receptor Blocking Agents

Beta-blockers not only block the pulmonary effect of beta-agonists, such as VENTOLIN HFA, but may also produce severe bronchospasm in patients with asthma. Therefore, patients with asthma should not normally be treated with beta-blockers. However, under certain circumstances, there may be no acceptable alternatives to the use of beta-adrenergic blocking agents for these patients; cardioselective beta-blockers could be considered, although they should be administered with caution.

7.2 Non–Potassium-Sparing Diuretics

The ECG changes and/or hypokalemia that may result from the administration of non–potassium-sparing diuretics (such as loop or thiazide diuretics) can be acutely worsened by beta-agonists, especially when the recommended dose of the beta-agonist is exceeded. Although the clinical significance of these effects is not known, caution is advised in the coadministration of VENTOLIN HFA with non–potassium-sparing diuretics.

7.3 Digoxin

Mean decreases of 16% to 22% in serum digoxin levels were demonstrated after single-dose intravenous and oral administration of albuterol, respectively, to normal volunteers who had received digoxin for 10 days. The clinical relevance of these findings for patients with obstructive airway disease who are receiving inhaled albuterol and digoxin on a chronic basis is unclear. Nevertheless, it would be prudent to carefully evaluate the serum digoxin levels in patients who are currently receiving digoxin and albuterol.

7.4 Monoamine Oxidase Inhibitors and Tricyclic Antidepressants

VENTOLIN HFA should be administered with extreme caution to patients being treated with monoamine oxidase inhibitors or tricyclic antidepressants, or within 2 weeks of discontinuation of such agents, because the action of albuterol on the vascular system may be potentiated.

8 USE IN SPECIFIC POPULATIONS

8.1 Pregnancy

Pregnancy Exposure Registry

There is a pregnancy exposure registry that monitors pregnancy outcomes in women exposed to asthma medications during pregnancy. For more information, contact the MotherToBaby Pregnancy Studies conducted by the Organization of Teratology Information Specialists at 1‑877-311-8972 or visit https://mothertobaby.org/ongoing-study/asthma.

Risk Summary

There are no randomized clinical studies of use of albuterol sulfate during pregnancy. Available data from epidemiological studies and postmarketing case reports of pregnancy outcomes following inhaled albuterol use do not consistently demonstrate a risk of major birth defects or miscarriage. There are, however, clinical considerations in pregnant women with asthma. (See Clinical Considerations.)

Administration of VENTOLIN HFA to mice and rabbits during the period of organogenesis revealed evidence of adverse developmental outcomes (cleft palate in mice, delayed ossification in rabbits) at less than the maximum recommended human daily inhaled dose (MRHDID). (See Data.)

The estimated background risk of major birth defects and miscarriage for the indicated population(s) is unknown. In the U.S. general population, the estimated risk of major birth defects and miscarriage in clinically recognized pregnancies is 2% to 4% and 15% to 20%, respectively.

Clinical Considerations

Disease-Associated Maternal and/or Embryofetal Risk:In women with poorly or moderately controlled asthma, there is an increased risk of several perinatal adverse outcomes such as preeclampsia in the mother and prematurity, low birth weight, and small for gestational age in the neonate. Pregnant women with asthma should be closely monitored and medication adjusted as necessary to maintain optimal asthma control.

Labor or Delivery:Because of the potential for beta-agonist interference with uterine contractility, use of VENTOLIN HFA during labor should be restricted to those patients in whom the benefits clearly outweigh the risk. VENTOLIN HFA has not been approved for the management of pre-term labor. Serious adverse reactions, including pulmonary edema, have been reported during or following treatment of premature labor with beta2-agonists, including albuterol.

Data

Human Data:While available studies cannot definitively establish the absence of risk, published data from epidemiological studies and case reports have not consistently demonstrated an association with use of VENTOLIN HFA during pregnancy and major birth defects, specific birth defects, or miscarriage. The available studies have methodologic limitations, including inconsistent comparator groups, definitions of outcomes, and assessment of disease impact.

Animal Data:In a study in pregnant mice, subcutaneously administered albuterol sulfate produced cleft palate formation in 5 of 111 (4.5%) fetuses at an exposure less than the MRHDID for adults (on a mg/m^2basis at a maternal dose of 0.25 mg/kg) and in 10 of 108 (9.3%) fetuses at approximately 9 times the MRHDID (on a mg/m^2basis at a maternal dose of 2.5 mg/kg). Cleft palate also occurred in 22 of 72 (30.5%) fetuses from females treated subcutaneously with isoproterenol, another beta2-agonist.

In a study in pregnant rabbits, orally administered albuterol sulfate produced cranioschisis in 7 of 19 fetuses (37%) at approximately 750 times the MRHDID (on a mg/m^2basis at a maternal dose of 50 mg/kg).

In a study in pregnant rabbits, an albuterol/HFA-134a formulation administered by inhalation produced enlargement of the frontal portion of the fetal fontanelles at approximately one third of the MRHDID on a mg/m^2basis.

A study in which pregnant rats were dosed with radiolabeled albuterol sulfate demonstrated that drug-related material is transferred from the maternal circulation to the fetus.

8.2 Lactation

Risk Summary

There are no available data on the presence of albuterol or the components of VENTOLIN HFA in human milk, the effects on the breastfed child, or the effects on milk production. However, plasma levels of albuterol after inhaled therapeutic doses are low in humans, and if present in breast milk, are likely to be correspondingly low [see Clinical Pharmacology (12.3)]. The developmental and health benefits of breastfeeding should be considered along with the mother’s clinical need for VENTOLIN HFA and any potential adverse effects on the breastfed child from VENTOLIN HFA or from the underlying maternal condition.

8.4 Pediatric Use

The safety and effectiveness of VENTOLIN HFA for treatment or prevention of bronchospasm and for prevention of exercised-induced bronchospasm in pediatric patients aged 4 years and older have been established. Use of VENTOLIN HFA for this indication is supported by evidence from adequate and well-controlled studies of two 12-week clinical trials in subjects aged 12 years and older with asthma and one 2-week clinical trial in subjects aged 4 to 11 years with asthma [see Adverse Reactions (6.1), Clinical Studies (14.1)].

The safety and effectiveness of VENTOLIN HFA in pediatric patients younger than 4 years have not been established. Three trials have been conducted to evaluate the safety and efficacy of VENTOLIN HFA in subjects younger than 4 years and the findings are described below.

Two 4-week randomized, double-blind, placebo-controlled trials were conducted in 163 pediatric subjects aged from birth to 48 months with symptoms of bronchospasm associated with obstructive airway disease (presenting symptoms included: wheeze, cough, dyspnea, or chest tightness). VENTOLIN HFA or placebo HFA was delivered with either an AeroChamber Plus Valved Holding Chamber or an Optichamber Valved Holding Chamber with mask 3 times daily. In one trial, VENTOLIN HFA 90 mcg (n = 26), VENTOLIN HFA 180 mcg (n = 25), and placebo HFA (n = 26) were administered to children aged between 24 and 48 months. In the second trial, VENTOLIN HFA 90 mcg (n = 29), VENTOLIN HFA 180 mcg (n = 29), and placebo HFA (n = 28) were administered to children aged between birth and 24 months. Over the 4-week treatment period, there were no treatment differences in asthma symptom scores between the groups receiving VENTOLIN HFA 90 mcg, VENTOLIN HFA 180 mcg, and placebo in either trial.

In a third trial, VENTOLIN HFA was evaluated in 87 pediatric subjects younger than 24 months for the treatment of acute wheezing. VENTOLIN HFA was delivered with an AeroChamber Plus Valved Holding Chamber in this trial. There were no significant differences in asthma symptom scores and mean change from baseline in an asthma symptom score between VENTOLIN HFA 180 mcg and VENTOLIN HFA 360 mcg.

In vitro dose characterization studies were performed to evaluate the delivery of VENTOLIN HFA via holding chambers with attached masks. The studies were conducted with 2 different holding chambers with masks (small and medium size). The in vitro study data when simulating patient breathing suggest that the dose of VENTOLIN HFA presented for inhalation via a valved holding chamber with mask will be comparable to the dose delivered in adults without a spacer and mask per kilogram of body weight (Table 2). However, clinical trials in children younger than 4 years described above suggest that either the optimal dose of VENTOLIN HFA has not been defined in this age group or VENTOLIN HFA is not effective in this age group. The safety and effectiveness of VENTOLIN HFA administered with or without a spacer device in children younger than 4 years have not been demonstrated.

Table 2. In Vitro Medication Delivery through AeroChamber Plus Valved Holding Chamber with a Mask
Age | Mask | Flow Rate (L/min) | Holding Time (seconds) | Mean Medication Delivery through AeroChamber Plus (mcg/actuation) | Body Weight 50thPercentile (kg)a | Medication Delivered per Actuation (mcg/kg)b
6 to 12 Months | Small | 4.9 | 0 | 18.2 | 7.5-9.9 | 1.8-2.4
 |  |  | 2 | 19.8 |  | 2.0-2.6
 |  |  | 5 | 13.8 |  | 1.4-1.8
 |  |  | 10 | 15.4 |  | 1.6-2.1
2 to 5 Years | Small | 8.0 | 0 | 17.8 | 12.3-18.0 | 1.0-1.4
 |  |  | 2 | 16.0 |  | 0.9-1.3
 |  |  | 5 | 16.3 |  | 0.9-1.3
 |  |  | 10 | 18.3 |  | 1.0-1.5
2 to 5 Years | Medium | 8.0 | 0 | 21.1 | 12.3-18.0 | 1.2-1.7
 |  |  | 2 | 15.3 |  | 0.8-1.2
 |  |  | 5 | 18.3 |  | 1.0-1.5
 |  |  | 10 | 18.2 |  | 1.0-1.5
>5 Years | Medium | 12.0 | 0 | 26.8 | 18.0 | 1.5
 |  |  | 2 | 20.9 |  | 1.2
 |  |  | 5 | 19.6 |  | 1.1
 |  |  | 10 | 20.3 |  | 1.1
a Centers for Disease Control growth charts, developed by the National Center for Health Statistics in collaboration with the National Center for Chronic Disease Prevention and Health Promotion (2000). Ranges correspond to the average of the 50th percentile weight for boys and girls at the ages indicated.
b A single inhalation of VENTOLIN HFA in a 70-kg adult without use of a valved holding chamber and mask delivers approximately 90 mcg, or 1.3 mcg/kg.

8.5 Geriatric Use

Clinical trials of VENTOLIN HFA did not include sufficient numbers of subjects aged 65 years and older to determine whether older subjects respond differently than younger subjects. Other reported clinical experience has not identified differences in responses between the elderly and younger patients. In general, dose selection for an elderly patient should be cautious, usually starting at the low end of the dosing range, reflecting the greater frequency of decreased hepatic, renal, or cardiac function, and of concomitant disease or other drug therapy.

10 OVERDOSAGE

The expected signs and symptoms with overdosage of albuterol are those of excessive beta-adrenergic stimulation and/or occurrence or exaggeration of any of the signs and symptoms of beta-adrenergic stimulation (e.g., seizures, angina, hypertension or hypotension, tachycardia with rates up to 200 beats/min, arrhythmias, nervousness, headache, tremor, muscle cramps, dry mouth, palpitation, nausea, dizziness, fatigue, malaise, insomnia, hyperglycemia, hypokalemia, metabolic acidosis).

As with all inhaled sympathomimetic medicines, cardiac arrest and even death may be associated with an overdose of VENTOLIN HFA.

Treatment consists of discontinuation of VENTOLIN HFA together with appropriate symptomatic therapy. The judicious use of a cardioselective beta-receptor blocker may be considered, bearing in mind that such medication can produce bronchospasm. There is insufficient evidence to determine if dialysis is beneficial for overdosage of VENTOLIN HFA.

11 DESCRIPTION

The active component of VENTOLIN HFA is albuterol sulfate, USP, the racemic form of albuterol and a relatively selective beta2-adrenergic bronchodilator. Albuterol sulfate has the chemical name α^1-[(tert-butylamino)methyl]-4-hydroxy- m-xylene-α, α′-diol sulfate (2:1)(salt) and the following chemical structure:

Albuterol sulfate is a white crystalline powder with a molecular weight of 576.7, and the empirical formula is (C13H21NO3)2•H2SO4. It is soluble in water and slightly soluble in ethanol.

The World Health Organization recommended name for albuterol base is salbutamol.

VENTOLIN HFA is a blue plastic inhaler with a blue cap containing a pressurized metered-dose aerosol canister fitted with a counter. Each canister contains a microcrystalline suspension of albuterol sulfate in propellant HFA-134a (1,1,1,2-tetrafluoroethane). It contains no other excipients.

After priming, each actuation of the inhaler delivers 120 mcg of albuterol sulfate, USP in 75 mg of suspension from the valve and 108 mcg of albuterol sulfate, USP from the mouthpiece (equivalent to 90 mcg of albuterol base from the mouthpiece).

Prime VENTOLIN HFA before using for the first time, when the inhaler has not been used for more than 2 weeks, or when the inhaler has been dropped. To prime VENTOLIN HFA, release 4 sprays into the air away from the face, shaking well before each spray. Avoid spraying in eyes.

12 CLINICAL PHARMACOLOGY

12.1 Mechanism of Action

In vitro studies and in vivo pharmacologic studies have demonstrated that albuterol has a preferential effect on beta2-adrenergic receptors compared with isoproterenol. Although beta2-adrenoceptors are the predominant adrenergic receptors in bronchial smooth muscle and beta1-adrenoceptors are the predominant receptors in the heart, there are also beta2-adrenoceptors in the human heart comprising 10% to 50% of the total beta-adrenoceptors. The precise function of these receptors has not been established, but their presence raises the possibility that even selective beta2-agonists may have cardiac effects.

Activation of beta2-adrenergic receptors on airway smooth muscle leads to the activation of adenyl cyclase and to an increase in the intracellular concentration of cyclic-3′,5′-adenosine monophosphate (cyclic AMP). This increase of cyclic AMP leads to the activation of protein kinase A, which inhibits the phosphorylation of myosin and lowers intracellular ionic calcium concentrations, resulting in relaxation. Albuterol relaxes the smooth muscles of all airways, from the trachea to the terminal bronchioles. Albuterol acts as a functional antagonist to relax the airway irrespective of the spasmogen involved, thus protecting against all bronchoconstrictor challenges. Increased cyclic AMP concentrations are also associated with the inhibition of release of mediators from mast cells in the airway.

Albuterol has been shown in most controlled clinical trials to have more effect on the respiratory tract, in the form of bronchial smooth muscle relaxation, than isoproterenol at comparable doses while producing fewer cardiovascular effects. Controlled clinical studies and other clinical experience have shown that inhaled albuterol, like other beta-adrenergic agonist drugs, can produce a significant cardiovascular effect in some patients, as measured by pulse rate, blood pressure, symptoms, and/or electrocardiographic changes [see Warnings and Precautions (5.4)].

12.3 Pharmacokinetics

The systemic levels of albuterol are low after inhalation of recommended doses. A trial conducted in 12 healthy male and female subjects using a higher dose (1,080 mcg of albuterol base) showed that mean peak plasma concentrations of approximately 3 ng/mL occurred after dosing when albuterol was delivered using propellant HFA-134a. The mean time to peak concentrations (Tmax) was delayed after administration of VENTOLIN HFA (Tmax = 0.42 hours) as compared with CFC-propelled albuterol inhaler (Tmax = 0.17 hours). Apparent terminal plasma half-life of albuterol is approximately 4.6 hours. No further pharmacokinetic trials for VENTOLIN HFA were conducted in neonates, children, or elderly subjects.

13 NONCLINICAL TOXICOLOGY

13.1 Carcinogenesis, Mutagenesis, Impairment of Fertility

In a 2-year study in Sprague-Dawley rats, albuterol sulfate caused a dose-related increase in the incidence of benign leiomyomas of the mesovarium at and above dietary doses of 2 mg/kg (approximately 15 and 6 times the MRHDID for adults and children, respectively, on a mg/m^2basis). In another study this effect was blocked by the coadministration of propranolol, a non-selective beta-adrenergic antagonist. In an 18-month study in CD-1 mice, albuterol sulfate showed no evidence of tumorigenicity at dietary doses of up to 500 mg/kg (approximately 1,900 and 740 times the MRHDID for adults and children, respectively, on a mg/m^2basis). In a 22-month study in Golden hamsters, albuterol sulfate showed no evidence of tumorigenicity at dietary doses of up to 50 mg/kg (approximately 250 and 100 times the MRHDID for adults and children, respectively, on a mg/m^2basis).

Albuterol sulfate was not mutagenic in the Ames test or a mutation test in yeast. Albuterol sulfate was not clastogenic in a human peripheral lymphocyte assay or in an AH1 strain mouse micronucleus assay.

Fertility and reproductive performance in rats demonstrated no evidence of impaired fertility at oral doses up to 50 mg/kg (approximately 380 times the MRHDID for adults on a mg/m^2basis).

13.2 Animal Toxicology and/or Pharmacology

Intravenous studies in rats with albuterol sulfate have demonstrated that albuterol crosses the blood-brain barrier and reaches brain concentrations amounting to approximately 5% of the plasma concentrations. In structures outside the blood-brain barrier (pineal and pituitary glands), albuterol concentrations were found to be 100 times those in the whole brain.

Studies in laboratory animals (minipigs, rodents, and dogs) have demonstrated the occurrence of cardiac arrhythmias and sudden death (with histologic evidence of myocardial necrosis) when beta-agonists and methylxanthines are administered concurrently. The clinical relevance of these findings is unknown.

14 CLINICAL STUDIES

14.1 Bronchospasm Associated with Asthma

Adult and Adolescent Subjects Aged 12 Years and Older

The efficacy of VENTOLIN HFA was evaluated in two 12-week, randomized, double-blind, placebo-controlled trials in subjects aged 12 years and older with mild to moderate asthma. These trials included a total of 610 subjects (323 males, 287 females). In each trial, subjects received 2 inhalations of VENTOLIN HFA, CFC 11/12-propelled albuterol, or HFA-134a placebo 4 times daily for 12 weeks’ duration. Subjects taking the HFA-134a placebo inhaler also took VENTOLIN HFA for asthma symptom relief on an as-needed basis. Some subjects who participated in these clinical trials were using concomitant inhaled steroid therapy. Efficacy was assessed by serial forced expiratory volume in 1 second (FEV1). In each of these trials, 2 inhalations of VENTOLIN HFA produced significantly greater improvement in FEV1over the pretreatment value than placebo. Results from the 2 clinical trials are described below.

In a 12-week, randomized, double-blind trial, VENTOLIN HFA (101 subjects) was compared with CFC 11/12-propelled albuterol (99 subjects) and an HFA-134a placebo inhaler (97 subjects) in adolescent and adult subjects aged 12 to 76 years with mild to moderate asthma. Serial FEV1measurements [shown below as percent change from test-day baseline at Day 1 (n = 297) and at Week 12 (n = 249)] demonstrated that 2 inhalations of VENTOLIN HFA produced significantly greater improvement in FEV1over the pretreatment value than placebo.

FEV1as Percent Change from Predose in a Large, 12-Week Clinical Trial

Day 1

Week 12

In the responder population (≥15% increase in FEV1within 30 minutes postdose) treated with VENTOLIN HFA, the mean time to onset of a 15% increase in FEV1over the pretreatment value was 5.4 minutes, and the mean time to peak effect was 56 minutes. The mean duration of effect as measured by a 15% increase in FEV1over the pretreatment value was approximately 4 hours. In some subjects, duration of effect was as long as 6 hours.

The second 12-week randomized, double-blind trial was conducted to evaluate the efficacy and safety of switching subjects from CFC 11/12-propelled albuterol to VENTOLIN HFA. During the 3-week run-in phase of the trial, all subjects received CFC 11/12-propelled albuterol. During the double-blind treatment phase, VENTOLIN HFA (91 subjects) was compared to CFC 11/12-propelled albuterol (100 subjects) and an HFA-134a placebo inhaler (95 subjects) in adult and adolescent subjects with mild to moderate asthma. Serial FEV1measurements demonstrated that 2 inhalations of VENTOLIN HFA produced significantly greater improvement in pulmonary function than placebo. The switching from CFC 11/12-propelled albuterol inhaler to VENTOLIN HFA did not reveal any clinically significant changes in the efficacy profile.

In the 2 adult trials, the efficacy results from VENTOLIN HFA were significantly greater than placebo and were clinically comparable to those achieved with CFC 11/12-propelled albuterol, although small numerical differences in mean FEV1response and other measures were observed. Physicians should recognize that individual responses to beta-adrenergic agonists administered via different propellants may vary and that equivalent responses in individual patients should not be assumed.

Pediatric Subjects Aged 4 to 11 Years

The efficacy of VENTOLIN HFA was evaluated in one 2-week, randomized, double-blind, placebo-controlled trial in 135 pediatric subjects aged 4 to 11 years with mild to moderate asthma. In this trial, subjects received VENTOLIN HFA, CFC 11/12-propelled albuterol, or HFA-134a placebo. Serial pulmonary function measurements demonstrated that 2 inhalations of VENTOLIN HFA produced significantly greater improvement in pulmonary function than placebo and that there were no significant differences between the groups treated with VENTOLIN HFA and CFC 11/12-propelled albuterol. In the responder population treated with VENTOLIN HFA, the mean time to onset of a 15% increase in peak expiratory flow rate (PEFR) over the pretreatment value was 7.8 minutes, and the mean time to peak effect was approximately 90 minutes. The mean duration of effect as measured by a 15% increase in PEFR over the pretreatment value was greater than 3 hours. In some subjects, duration of effect was as long as 6 hours.

14.2 Exercise-Induced Bronchospasm

One controlled clinical trial in adult subjects with asthma (N = 24) demonstrated that 2 inhalations of VENTOLIN HFA taken approximately 30 minutes prior to exercise significantly prevented exercise-induced bronchospasm (as measured by maximum percentage fall in FEV1following exercise) compared with an HFA-134a placebo inhaler. In addition, VENTOLIN HFA was shown to be clinically comparable to a CFC 11/12-propelled albuterol inhaler for this indication.

16 HOW SUPPLIED/STORAGE AND HANDLING

VENTOLIN HFA is supplied in the following boxes of 1 as a pressurized aluminum canister fitted with a counter and supplied with a blue plastic actuator with a blue cap:

NDC: 70518-1081-00

PACKAGING: 1 in 1 CARTON, 200 in 1 INHALER, TYPE 2

The blue actuator supplied with VENTOLIN HFA should not be used with any other product canisters, and actuators from other products should not be used with a VENTOLIN HFA canister.

Counter

VENTOLIN HFA has a counter attached to the canister. The counter starts at 204 or 064 and counts down each time a spray is released. The correct amount of medication in each actuation cannot be assured after the counter reads 000, even though the canister is not completely empty and will continue to operate. The inhaler should be discarded when the counter reads 000.

Contents under Pressure

Do not puncture. Do not use or store near heat or open flame. Exposure to temperatures above 120°F may cause bursting. Never throw canister into fire or incinerator.

Storage

Store at room temperature between 68°F and 77°F (20°C and 25°C); excursions permitted from 59°F to 86°F (15°C to 30°C) [See USP Controlled Room Temperature]. Store the inhaler with the mouthpiece down. For best results, the inhaler should be at room temperature before use.

Repackaged and Distributed By:

Remedy Repack, Inc.

625 Kolter Dr. Suite #4 Indiana, PA 1-724-465-8762

17 PATIENT COUNSELING INFORMATION

Advise the patient to read the FDA-approved patient labeling (Patient Information and Instructions for Use).

Frequency of Use

Inform patients that the action of VENTOLIN HFA should last up to 4 to 6 hours. Do not use VENTOLIN HFA more frequently than recommended. Instruct patients not to increase the dose or frequency of doses of VENTOLIN HFA without consulting the physician. Instruct patients to seek medical attention immediately if treatment with VENTOLIN HFA becomes less effective for symptomatic relief, symptoms become worse, and/or they need to use the product more frequently than usual.

Priming

Instruct patients to prime VENTOLIN HFA before using for the first time, when the inhaler has not been used for more than 2 weeks, or when the inhaler has been dropped. To prime VENTOLIN HFA, release 4 sprays into the air away from the face, shaking well before each spray. Avoid spraying in eyes.

Cleaning

To ensure proper dosing and to prevent actuator orifice blockage, instruct patients to wash the actuator with warm water and let it air-dry completely at least once a week. Inform patients that detailed cleaning instructions are included in the Patient Information leaflet.

Paradoxical Bronchospasm

Inform patients that VENTOLIN HFA can produce paradoxical bronchospasm. Instruct them to discontinue VENTOLIN HFA if paradoxical bronchospasm occurs [see Warnings and Precautions (5.1)].

Concomitant Drug Use

Advise patients that while they are using VENTOLIN HFA, other inhaled drugs and asthma medications should be taken only as directed by the physician.

Common Adverse Effects

Common adverse effects of treatment with inhaled albuterol include palpitations, chest pain, rapid heart rate, tremor, and nervousness.

Pregnancy Exposure Registry

Inform women there is a pregnancy exposure registry that monitors pregnancy outcomes in women exposed to asthma medications, including VENTOLIN HFA, during pregnancy and that they can enroll in the Pregnancy Exposure Registry by calling 1-877-311-8972 or by visiting https://mothertobaby.org/ongoing-study/asthma [see Use in Specific Populations (8.1)].

VENTOLIN is owned by or licensed to the GSK group of companies.

Repackaged By / Distributed By: RemedyRepack Inc.

625 Kolter Drive, Indiana, PA 15701

(724) 465-8762

PATIENT INFORMATION

VENTOLIN (VENT o lin) HFA

(albuterol sulfate inhalation aerosol)

for oral inhalation use

What is VENTOLIN HFA?

- VENTOLIN HFA is a prescription inhaled medicine used in people aged 4 years and older to:
- treat or prevent bronchospasm in people who have reversible obstructive airway disease.
- prevent exercise-induced bronchospasm.
- It is not known if VENTOLIN HFA is safe and effective in children younger than 4 years of age.

Do not use VENTOLIN HFA:

- if you are allergic to albuterol sulfate propionate or any of the ingredients in VENTOLIN HFA. See the end of this Patient Information for a complete list of ingredients in VENTOLIN HFA.

Before using VENTOLIN HFA, tell your healthcare provider about all of your medical conditions, including if you:

- have heart problems.
- have high blood pressure.
- have seizures.
- have thyroid problems.
- have diabetes.
- have low potassium levels in your blood.
- are pregnant or plan to become pregnant. It is not known if VENTOLIN HFA may harm your unborn baby.
- Pregnancy Registry. There is a pregnancy registry for women with asthma who receive asthma medications, including VENTOLIN HFA, while pregnant. The purpose of the registry is to collect information about the health of you and your baby. You can talk to your healthcare provider about how to take part in this registry or you can get more information and register by calling 1-877-311-8972 or go to https://mothertobaby.org/ongoing-study/asthma.
- are breastfeeding. It is not known if the medicine in VENTOLIN HFA passes into your milk and if it can harm your baby.

Tell your healthcare provider about all the medicines you take,including prescription and over-the-counter medicines, vitamins, and herbal supplements. VENTOLIN HFA and certain other medicines may interact with each other. This may cause serious side effects. Especially tell your healthcare provider if you take:

- other inhaled medicines or asthma medicines
- beta-blocker medicines
- diuretics
- digoxin
- monoamine oxidase inhibitors
- tricyclic antidepressants

Know the medicines you take. Keep a list of them to show your healthcare provider and pharmacist when you get a new medicine.

How should I use VENTOLIN HFA?

Read the step-by-step instructions for using VENTOLIN HFA at the end of this Patient Information.

- Do notuse VENTOLIN HFA unless your healthcare provider has taught you how to use the inhaler and you understand how to use it correctly.
- Children should use VENTOLIN HFA with an adult’s help, as instructed by the child’s healthcare provider.
- Use VENTOLIN HFA exactly as your healthcare provider tells you to use it. Do notuse VENTOLIN HFA more often than prescribed.
- Do notincrease your dose or take extra doses of VENTOLIN HFA without first talking to your healthcare provider.
- Each dose of VENTOLIN HFA should last up to 4 hours to 6 hours.
- Get medical help right away if VENTOLIN HFA no longer helps your symptoms.
- Get medical help right away if your symptoms get worse or if you need to use your inhaler more often.
- While you are using VENTOLIN HFA, use other inhaled medicines and asthma medicines only as directed by your healthcare provider.
- Call your healthcare provider if your asthma symptoms like wheezing and trouble breathing become worse over a few hours or days. Your healthcare provider may need to give you another medicine to treat your symptoms.

What are the possible side effects of VENTOLIN HFA?

VENTOLIN HFA can cause serious side effects, including:

- worsening trouble breathing, coughing, and wheezing (paradoxical bronchospasm).If this happens, stop using VENTOLIN HFA and call your healthcare provider or get emergency help right away. Paradoxical bronchospasm is more likely to happen with your first use of a new canister of medicine.
- heart problems, including faster heart rate and higher blood pressure.
- possible death in people with asthma who use too much VENTOLIN HFA.
- serious allergic reactions.Call your healthcare provider or get emergency medical care if you get any of the following symptoms of a serious allergic reaction:
- ο rash ο swelling of your face, mouth, and tongue
- ο hives ο breathing problems

- changes in laboratory blood levels (sugar, potassium).

Common side effects of VENTOLIN HFA include:

- • sore throat • chest pain
- • upper respiratory tract infection, including viral infection • fast heart rate
- • cough • shakiness
- • muscle pain • nervousness
- • your heart feels like it is pounding or racing (palpitations) • dizziness

These are not all the possible side effects of VENTOLIN HFA.

Call your doctor for medical advice about side effects. You may report side effects to FDA at 1-800-FDA-1088.

How should I store VENTOLIN HFA?

- Store VENTOLIN HFA at room temperature between 68°F and 77°F (20°C and 25°C) with the mouthpiece down.
- The contents of your VENTOLIN HFA are under pressure: Do notpuncture. Do notuse or store near heat or open flame. Temperatures above 120°F may cause the canister to burst.
- Do notthrow into fire or an incinerator.

Keep VENTOLIN HFA and all medicines out of the reach of children.

General information about the safe and effective use of VENTOLIN HFA.

Medicines are sometimes prescribed for purposes other than those listed in a Patient Information leaflet. Do not use VENTOLIN HFA for a condition for which it was not prescribed. Do not give VENTOLIN HFA to other people, even if they have the same symptoms that you have. It may harm them.

You can ask your healthcare provider or pharmacist for information about VENTOLIN HFA that was written for health professionals.

What are the ingredients in VENTOLIN HFA?

Active ingredient:albuterol sulfate

Inactive ingredient:propellant HFA-134a

- This Patient Information has been approved by the U.S. Food and Drug Administration Revised: April 2024

INSTRUCTIONS FOR USE

VENTOLIN (VENT o lin) HFA

(albuterol sulfate inhalation aerosol)

for oral inhalation use

Your VENTOLIN HFA inhaler

Figure A

- The metal canister holds the medicine. See Figure A.
- The metal canister has a counter to show how many sprays of medicine you have left. The number shows through a window in the back of the blue plastic actuator. See Figure A.

- The counter starts at either 204or 064, depending on which size inhaler you have. The number will count down by 1 each time you spray the inhaler. The counter will stop counting at 000.
- Do not try to change the numbers or take the counter off the metal canister.The counter cannot be reset, and it is permanently attached to the metal canister.
- The blue plastic actuator sprays the medicine from the metal canister. The plastic actuator has a blue protective cap that covers the mouthpiece. See Figure A.Keep the protective cap on the mouthpiece when the metal canister is not in use.
- Do notuse the plastic actuator with a canister of medicine from any other inhaler.
- Do notuse a VENTOLIN HFA metal canister with an actuator from any other inhaler.

Before using your VENTOLIN HFA inhaler

- The inhaler should be at room temperature before you use it.
- If your child needs to use VENTOLIN HFA, watch your child closely to make sure your child uses the inhaler correctly. Your healthcare provider will show you how your child should use VENTOLIN HFA.

Priming your VENTOLIN HFA inhaler

Figure B

Figure C

Figure D

- Before you use VENTOLIN HFA for the first time, you must prime the inhaler so that you will get the right amount of medicine when you use it.

- To take the cap off the mouthpiece, squeeze the sides of the cap and pull it straight out. See Figure B.
- Shake the inhaler well.
- Spray the inhaler 1 time into the air away from your face. Avoid spraying in eyes. See Figure C.
- Shake and spray the inhaler like this 3 more times to finish priming it. The counter should now read 200or 060, depending on which size inhaler you have. See Figure D.
- You must prime your inhaler again if you have not used it in more than 14 days or if you have dropped it. To take the cap off the mouthpiece, squeeze the sides of the cap and pull it straight out. Shake and spray the inhaler 4 times into the air away from your face.

How to use your VENTOLIN HFA inhaler

Follow these steps every time you use VENTOLIN HFA.

Figure E

Figure F

Figure G

1. Step 1.Make sure the metal canister fits firmly in the plastic actuator. The counter should show through the window in the actuator.
2. To take the cap off the mouthpiece, squeeze the sides of the cap and pull it straight out.
3. Look inside the mouthpiece for foreign objects and take out any you see.
4. Step 2.Hold the inhaler with the mouthpiece down and shake it well. See Figure E.
5. Step 3.Breathe out through your mouth and push as much air from your lungs as you can. See Figure F.
6. Step 4.Put the mouthpiece in your mouth and close your lips around it. Push the top of the metal canister firmly all the way downwhile you breathe in deeply and slowly through your mouth. See Figure G.
7. Step 5.After the spray comes out, take your finger off the metal canister. After you have breathed in all the way, take the inhaler out of your mouth and close your mouth.
8. Step 6. Hold your breath for about 10 seconds,or for as long as is comfortable. Breathe out slowly as long as you can.
9. If your healthcare provider has told you to use more sprays, wait 1 minute and shake the inhaler again. Repeat Step 2 through Step 6.
10. Put the cap back on the mouthpiece after you finish using the inhaler. Make sure it snaps firmly into place.

Cleaning your VENTOLIN HFA inhaler

Figure H

Figure I

Figure J

Figure K

Clean your inhaler at least 1 time each week. You may not see any medicine build-up on the inhaler, but it is important to keep it clean so medicine build-up will not block the spray. See Figure H.

1. Step 7.Take the canister out of the plastic actuator and take the cap off the mouthpiece by squeezing the sides of the cap and pulling it straight out.
2. Step 8.Hold the plastic actuator under the faucet and run warm water through it for about 30 seconds. See Figure I.
3. Step 9.Turn the plastic actuator upside down and run warm water through the mouthpiece for about 30 seconds. See Figure J.
4. Step 10.Shake off as much water from the plastic actuator as you can. Look into the mouthpiece to make sure any medicine build-up has been completely washed away. If there is any build-up, repeat Step 8 and Step 9.
5. Step 11.Let the plastic actuator air-dry overnight. See Figure K.
6. Step 12.When the plastic actuator is dry, put the protective cap on the mouthpiece and then put the canister in the plastic actuator and make sure it fits firmly. Shake the inhaler well, remove the cap, and spray the inhaler 1 time into the air away from your face. (The counter will count down by 1 number.) Put the cap back on the mouthpiece.

If you need to use your inhaler before the plastic actuator is completely dry:

- Shake as much water off the plastic actuator as you can.
- Put the cap on the mouthpiece and then put the canister in the plastic actuator and make sure it fits firmly.
- Shake the inhaler well, remove the cap, and spray it 1 time into the air away from your face.
- Take your VENTOLIN HFA dose as prescribed.
- Follow cleaning Step 7 through Step 12 above.

Replacing your VENTOLIN HFA inhaler

- When the counter reads 020, you should refill your prescription or ask your healthcare provider if you need another prescription for VENTOLIN HFA.
- When the counter reads 000, throw the inhaler away.You should not keep using the inhaler when the counter reads 000because you will not receive the right amount of medicine.
- Do not use the inhalerafter the expiration date, which is on the packaging it comes in.

For correct use of your VENTOLIN HFA inhaler, remember:

- The metal canister should always fit firmly in the plastic actuator.
- Breathe in deeply and slowly to make sure you get all the medicine.
- Hold your breath for about 10 seconds after breathing in the medicine. Then breathe out fully.
- Always keep the protective cap on the mouthpiece when your inhaler is not in use.
- Always store your inhaler with the mouthpiece pointing down.
- Clean your inhaler at least 1 time each week.

For more information about VENTOLIN HFA or how to use your inhaler, call 1-888-825-5249.

Repackaged and Distributed By:

Remedy Repack, Inc.

625 Kolter Dr. Suite #4 Indiana, PA 1-724-465-8762

- This Instructions for Use has been approved by the U.S. Food and Drug Administration Revised: April 2024

PACKAGE LABEL

DRUG: VENTOLINHFA HFA

GENERIC: albuterol sulfate

DOSAGE: AEROSOL, METERED

ADMINSTRATION: RESPIRATORY (INHALATION)

NDC: 70518-1081-0

PACKAGING:1 in 1 CARTON, 200 in 1 INHALER TYPE 2

ACTIVE INGREDIENT(S):

- ALBUTEROL SULFATE 90ug in 1

INACTIVE INGREDIENT(S):

- NORFLURANE